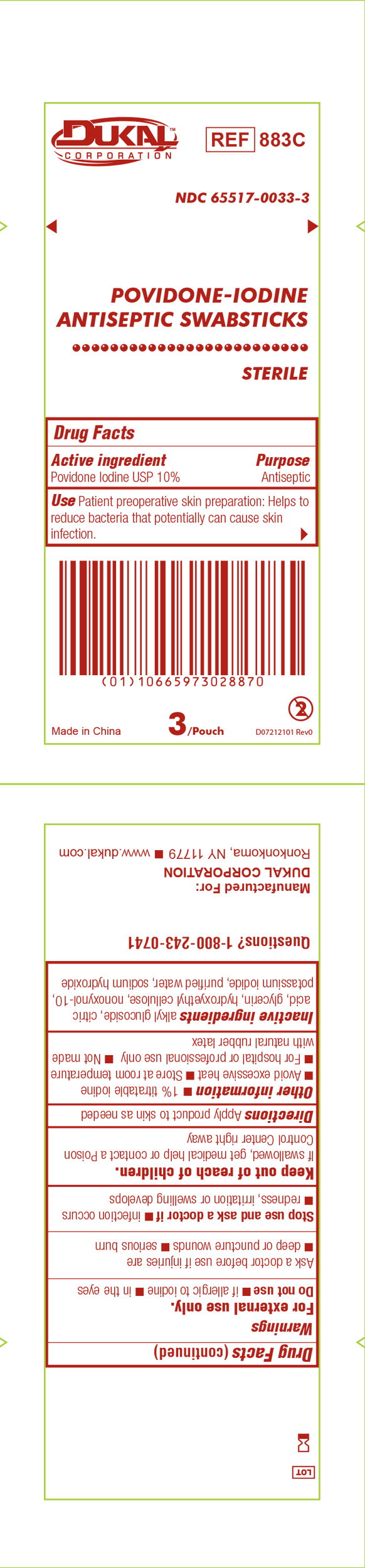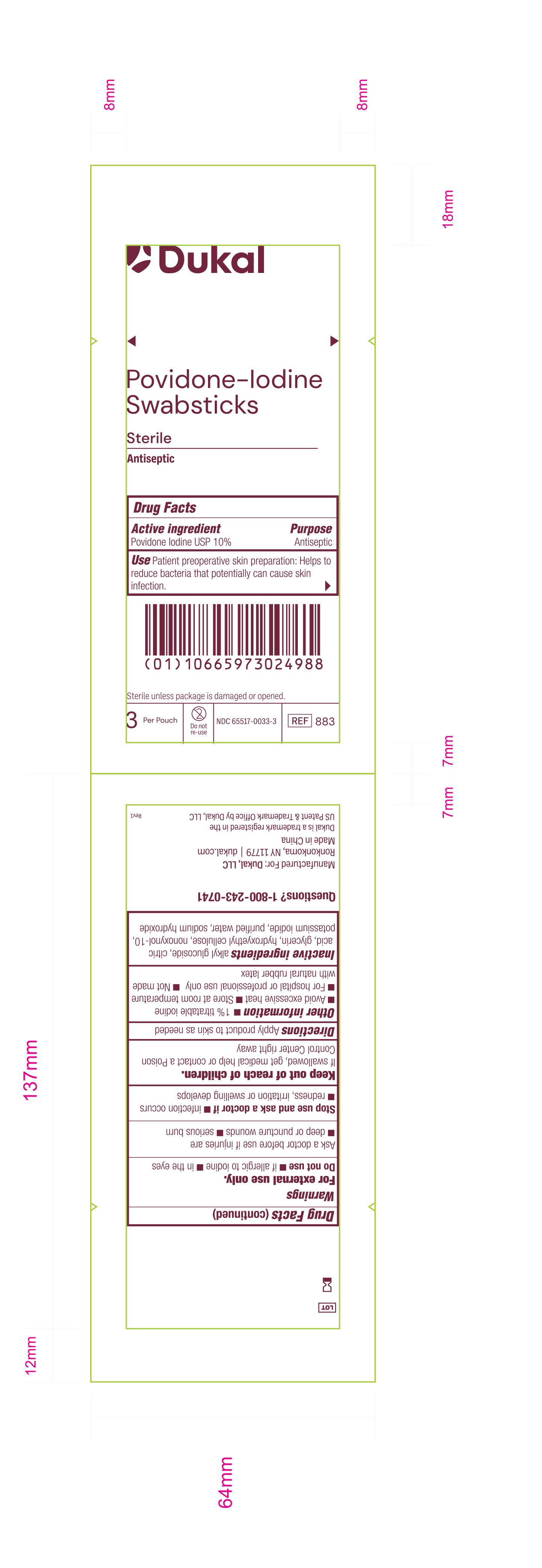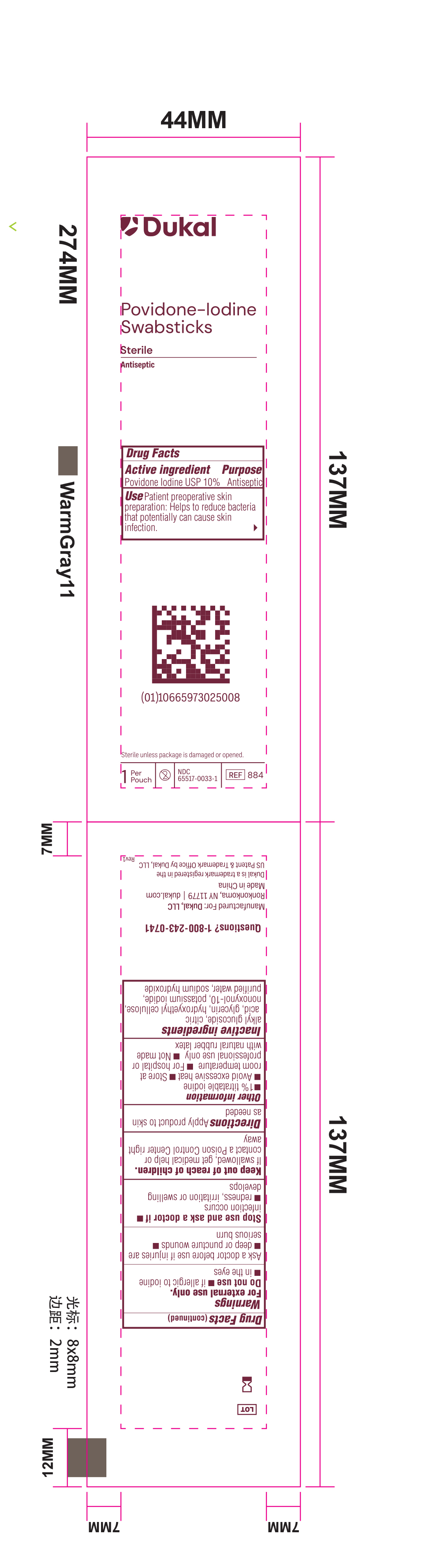 DRUG LABEL: PVP-Iodine Swabstick Threes
NDC: 65517-0033 | Form: SWAB
Manufacturer: Dukal LLC
Category: otc | Type: HUMAN OTC DRUG LABEL
Date: 20251119

ACTIVE INGREDIENTS: POVIDONE-IODINE 1 g/100 mL
INACTIVE INGREDIENTS: GLYCERIN; HYDROXYETHYL CELLULOSE (2000 MPA.S AT 1%); NONOXYNOL-10; ANHYDROUS CITRIC ACID; SODIUM HYDROXIDE; WATER; POTASSIUM IODIDE

65517-0033

Active Ingredient:

Povidone-Iodine USP 10%

Purpose:

Antiseptic

Use:

For preparation prior to surgery. Helps to reduce bacteria that can potentially cause skin infection.

Warnings:

For external use only.

- Do not apply to persons allergic to iodine. Do not use in the eyes.

- Ask a doctor before use if injuries are deep wounds, puncture wounds, serious burns.

- Stop use and ask a doctor if irritation and redness develop, condition persists for more than 72 hours, infection occurs.
- Avoid pooling beneath the patient. Prolonged exposure to wet solution may cause skin irritation.

- Keep out of reach of children
- If swallowed or gets in eyes, get medical help or contact a Poison Control Center right away.

Directions:

Clean the area. Apply product to the operative site prior to surgery using sponge sticks to prep desired area.

Other Information:

1% titratable iodine, for hospital or professional use only.

Store at ambient temperatures.

Inactive Ingredients:

Citric Acid, Glycerin, Sodium Hydroxide, Potassium Iodide, Alkyl Glucoside, Nonoxynol-10, Hydroxyethyl Cellulose and Purified Water.

Principal Display Panel - PVP-I Prep Swabstick Sterile 883 Pouch Label

Dukal
Povidone-Iodine

Swabstick

Sterile

Antiseptic

Drug Facts

Active Ingredient Purpose

Povidone Iodine USP 10% Antiseptic

Use Patient preoperative skin reparation: Helps to reduce bacteria that potentially can cause skin infection.

Sterile unless package is damaged or opened.

3 Per Pouch - Do not re-use - NDC 6551-0033-3 - REF 883

Principal Display Panel - PVP-I Prep Swabstick Sterile 884 Pouch Label

Dukal
Povidone-Iodine

Swabstick

Sterile

Antiseptic

Drug Facts

Active Ingredient Purpose

Povidone Iodine USP 10% Antiseptic

Use Patient preoperative skin reparation: Helps to reduce bacteria that potentially can cause skin infection.

Sterile unless package is damaged or opened.

1 Per Pouch - 2 - NDC 6551-0033-1 - REF 884

Principal Display Panel - PVP-I Prep Swabstick Sterile 883C Pouch Label

Dukal
Povidone-Iodine

Swabstick

Sterile

Antiseptic

Drug Facts

Active Ingredient Purpose

Povidone Iodine USP 10% Antiseptic

Use Patient preoperative skin reparation: Helps to reduce bacteria that potentially can cause skin infection.

Sterile unless package is damaged or opened.

3 Per Pouch - Do not re-use - NDC 6551-0033-3 - REF 883C